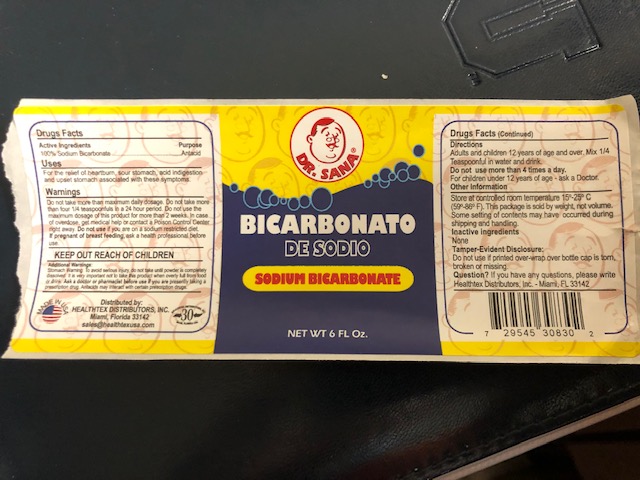 DRUG LABEL: Sodium Bicarbonate
NDC: 10095-100 | Form: POWDER
Manufacturer: World Perfumes Inc
Category: otc | Type: HUMAN OTC DRUG LABEL
Date: 20250115

ACTIVE INGREDIENTS: SODIUM BICARBONATE 2.6 g/2.6 g
INACTIVE INGREDIENTS: BICARBONATE ION 0.1 g/2.6 g

DR SANA SODIUM BICARBONATE 6oz

Active Ingredient(s)

Sodium Bicarbonate 100%. Purpose: Antacid

Purpose

Antacid

Use

For the relief of heartburn, sour stomach, acid ingestion and upset stomach associated with these symptoms.

Warnings

Do not take more than maximum daily dosage. Do not take more than four 1/4 teaspoonfuls in a 24 hour period. Do not use the maximum dosage of this product for more than 2 weeks. In case of overdose, get medical help or contact a Poison Control Center right away. Do not use if you are on a sodium restricted diet. If preganat of breast feeding, ask a health professional before use.

Do not use

- If you are on sodium restricted diet

KEEP OUT OF REACH OF CHILDREN

KEEP OUT REACH OF CHILDREN

Additional Warnings

Stomach Warning: To avoid serious injury, do not take until powder is completely dissolved. it is very important not to take this product when overly full from food or drink. Ask a doctor or pharmacist before use if you are presently taking a prescription drug. Antacids may interact with certain prescription drugs.

Directions

- Adults and children 12 years of age and over. Mix 1/4 Teaspoonful in water and drink.
- Do not use more than 4 times a day.
- For children under 12 years of age - ask a doctor

Other information

- Store at controlled room temperature 15- 25C (59- 86F)
- This package is sold by weight, not volume
- Some setting of contents may have occured during shipping and handling

Inactive ingredients

none

Tamper-Evident Disclosure:

Do nt use if over-wrap bottle cap is torn broken or missing.

Package Label - Principal Display Panel

6 fl oz